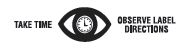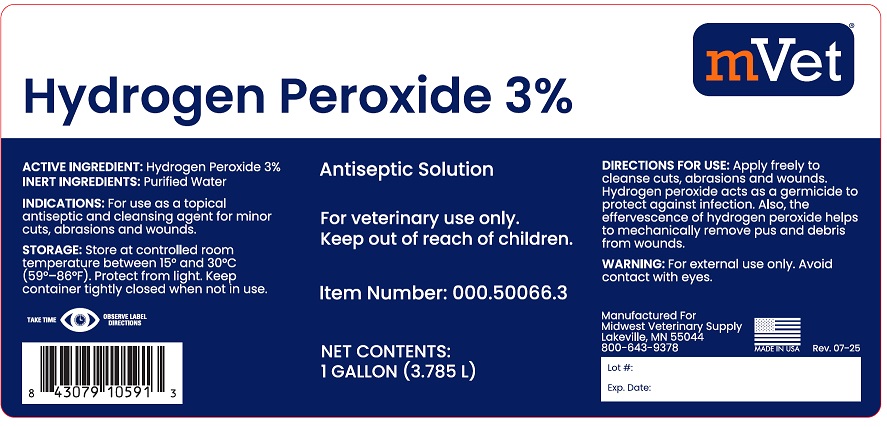 DRUG LABEL: Hydrogen Peroxide
NDC: 86223-025 | Form: SOLUTION
Manufacturer: Midwest Veterinary Supply, Inc.
Category: animal | Type: OTC ANIMAL DRUG LABEL
Date: 20250808

ACTIVE INGREDIENTS: HYDROGEN PEROXIDE 0.03 L/1 L

Hydrogen Peroxide 3%

Antiseptic Solution

For veterinary use only.

Keep out of reach of children.

NET CONTENTS: 1 GALLON (3.785 L)

ACTIVE INGREDIENT: Hydrogen Peroxide 3%

INACTIVE INGREDIENTS: Purified Water

INDICATIONS: For use as a topical antiseptic and cleansing agent for minor cuts, abrasions and wounds.

DIRECTIONS FOR USE: Apply freely to cleanse cuts, abrasions and wounds. Hydrogen peroxide act as germicide to protect against infection.Also, the effervescence of hydrogen peroxide helps to mechanically remove pus and debris from wounds.

STORAGE: Store at controlled room temperature between 15º and 30ºC (59º-86ºF). Protect from light. Keep container tightly closed when not in use.

WARNING: For external use only. Avoid contact with eyes.

Manufactured for

Midwest Veterinary Supply

Lakeville, MN 55044

MADE IN USA